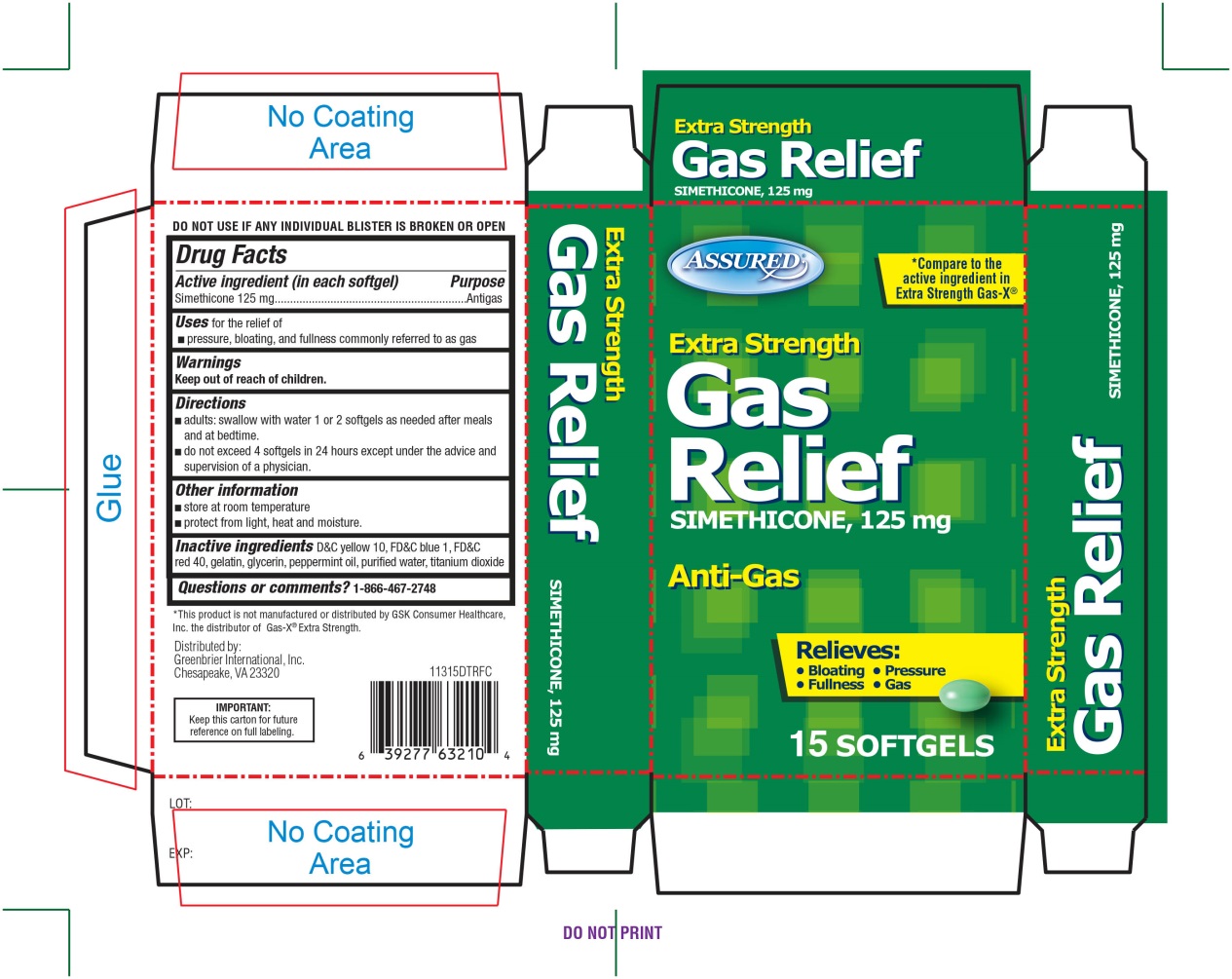 DRUG LABEL: Extra Strength Gas Relief
NDC: 33992-3113 | Form: CAPSULE, LIQUID FILLED
Manufacturer: Greenbrier International, Inc.
Category: otc | Type: HUMAN OTC DRUG LABEL
Date: 20171221

ACTIVE INGREDIENTS: DIMETHICONE 125 mg/1 1
INACTIVE INGREDIENTS: D&C YELLOW NO. 10; FD&C BLUE NO. 1; FD&C RED NO. 40; GELATIN; GLYCERIN; PEPPERMINT OIL; WATER; TITANIUM DIOXIDE

Extra Strength Gas Relief Simethicone, 125 mg Anti-Gas 15 Softgels

Active ingredient (per each softgel)

Simethicone 125 mg

Purpose

Antigas

Use

for the relief of

- Pressure, bloating, and fullness commonly referred to as gas

Directions

- adults: swallow with water 1 or 2 softgels as needed after meals and at bedtime.
- do not exceed 4 softgels in 24 hours except under the advice and supervision of a physician.

Other information

- store at room temperature
- protect from light, heat, and moisture

Inactive ingredients

D&C yellow 10, FD&C blue 1, FD&C red 40, gelatin, glycerin, peppermint oil, purified water, titanium dioxide

Questions or comments

1-866-467-2748

Principal Display Panel

*Compare to the active ingredient in Extra Strength Gas-X®

Assured

Extra Strength

Gas Relief

SIMETHICONE, 125mg

ANTI-GAS

Relieves:

- Bloating
- Pressure
- Fullness
- Gas
  15 SOFTGELS

*This product is not manufactured or distributed by GSK Consumer Healthcare, Inc., the distributor of Gas-X® Extra strength.
Distributed by:

Greenbrier International, Inc.

Chesapeake, VA 23320

IMPORTANT: Keep this carton for future reference on full labeling.

DO NOT USE IF ANY INDIVIDUAL BLISTER IS BROKEN OR OPEN